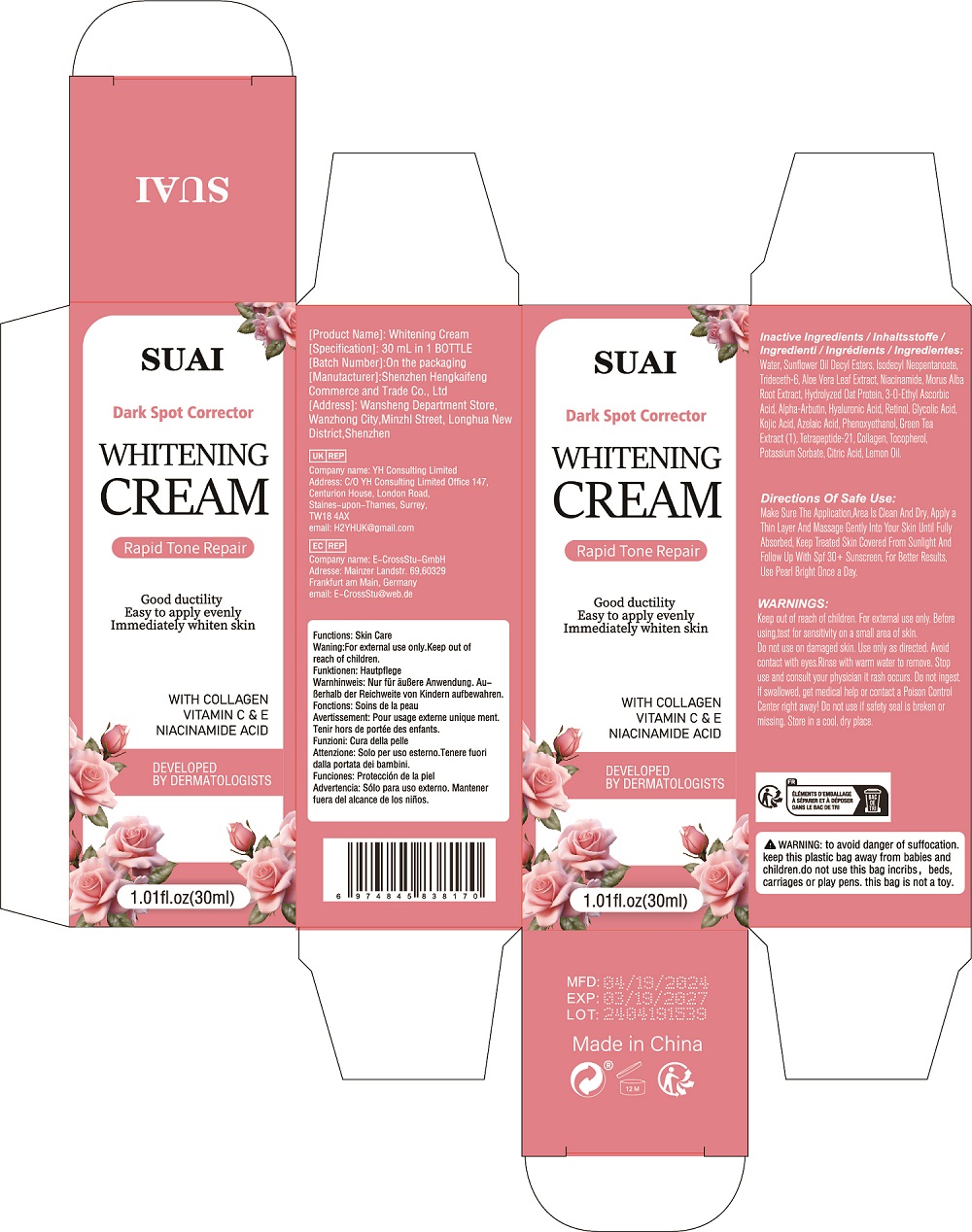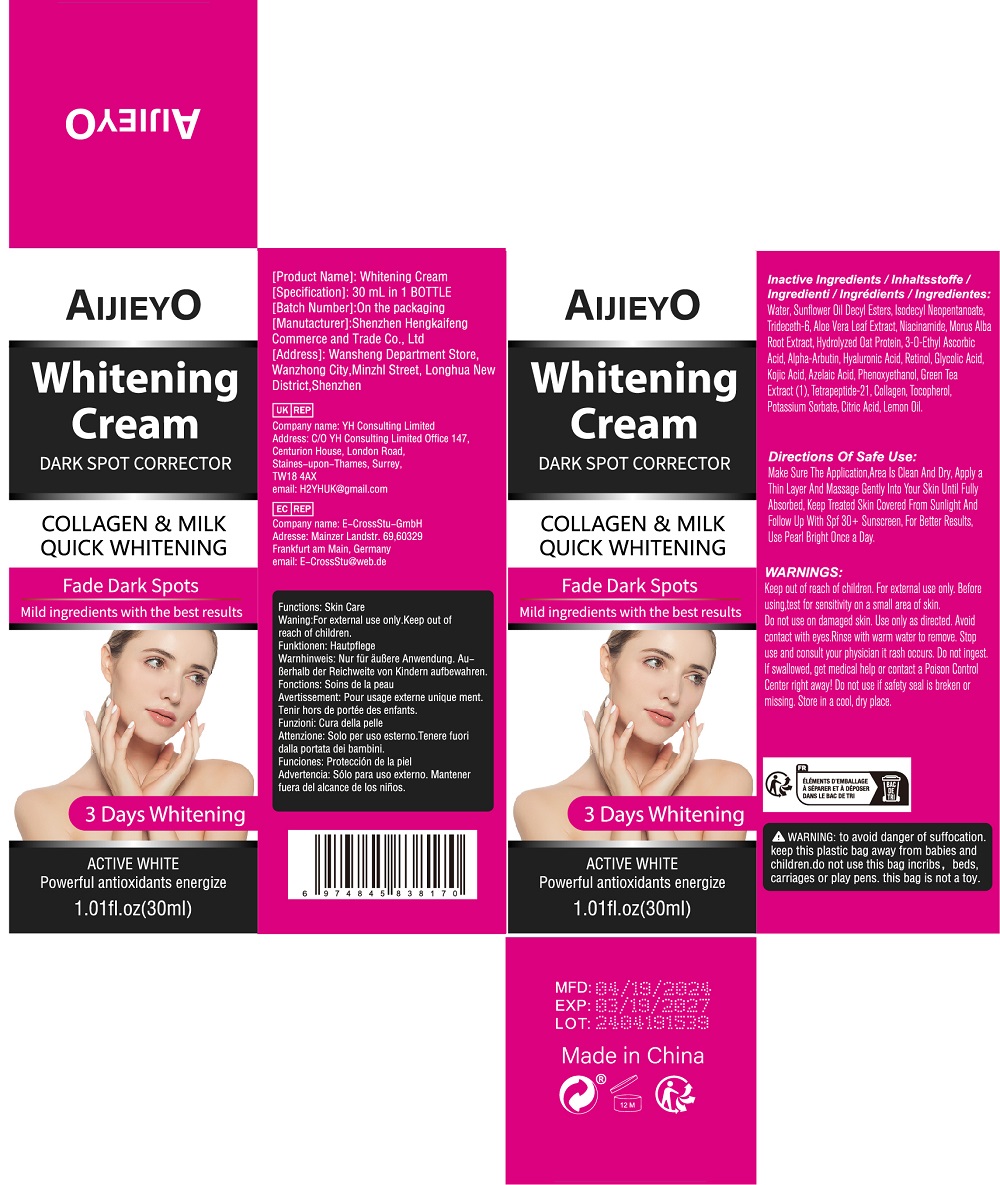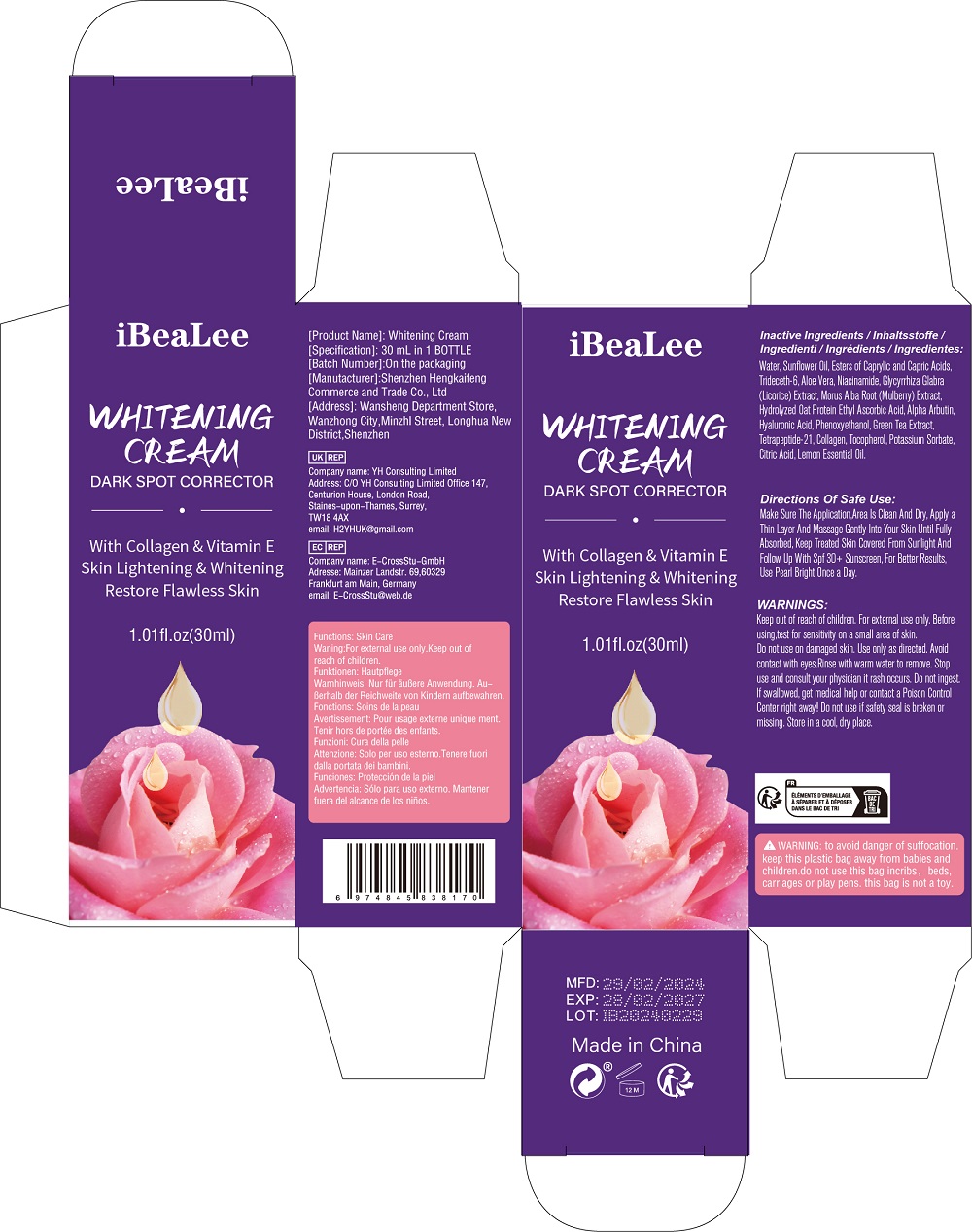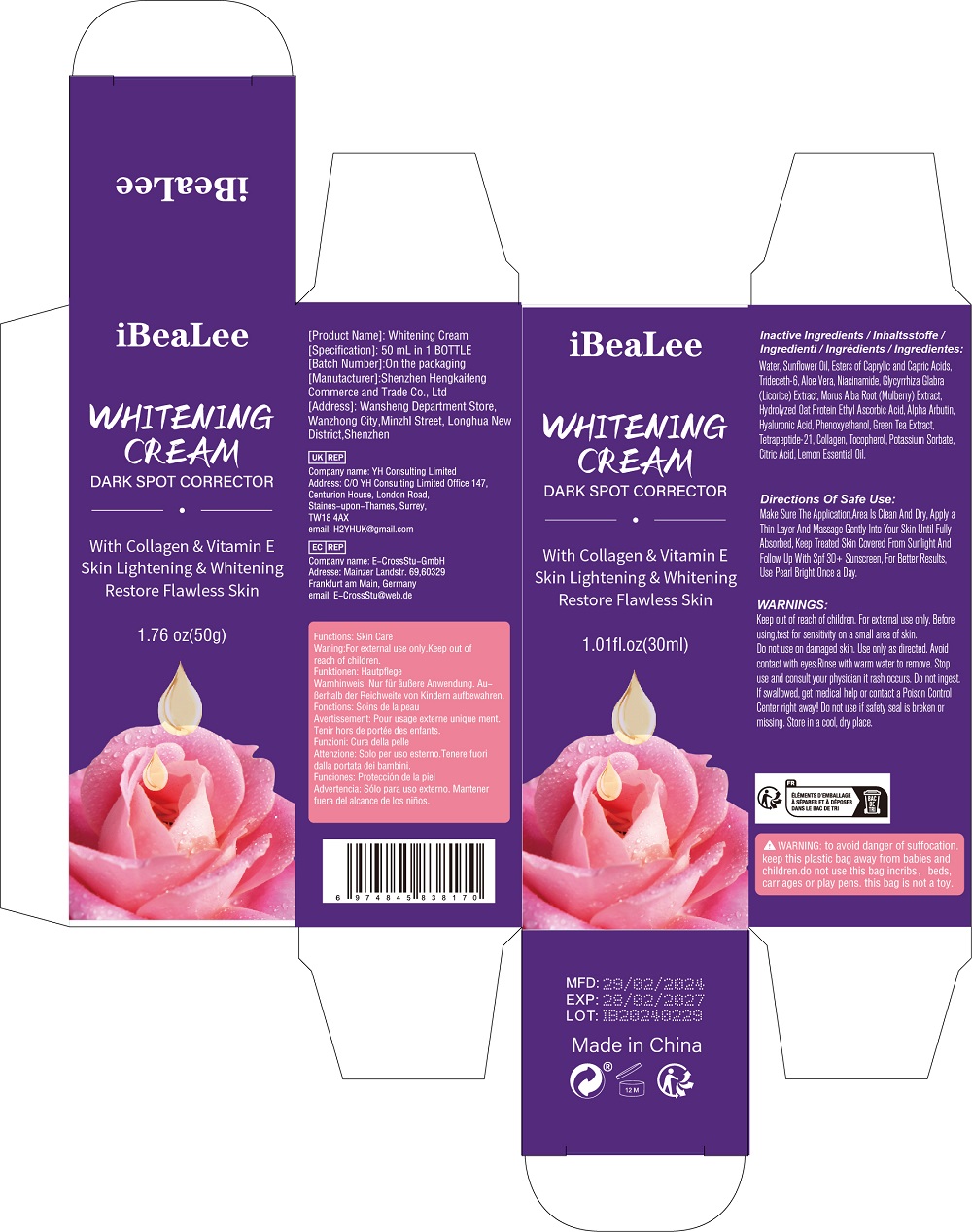 DRUG LABEL: Whitening Cream
NDC: 84117-007 | Form: CREAM
Manufacturer: Shenzhen Hengkaifeng Commerce and Trade Co., Ltd
Category: otc | Type: HUMAN OTC DRUG LABEL
Date: 20240428

ACTIVE INGREDIENTS: ALPHA-ARBUTIN 2 g/100 mL
INACTIVE INGREDIENTS: POTASSIUM SORBATE; GREEN TEA LEAF; ATELOCOLLAGEN; CITRIC ACID MONOHYDRATE; LEMON OIL; TOCOPHEROL; TETRAPEPTIDE-21; WATER; SUNFLOWER OIL; OCTANOIC ACID; TRIDECETH-6; ALOE VERA LEAF; NIACINAMIDE; GLYCYRRHIZA GLABRA; MORUS ALBA ROOT; 3-O-ETHYL ASCORBIC ACID; HYALURONIC ACID; PHENOXYETHANOL

ACTIVE INGREDIENT

Alpha Arbutin 2%

Purpose

Whitening Skin

Use

Skin Lightening & Whitening Restore Flawless Skin

Warnings

Keep out of reach of children. For external use only. Before
using,test for sensitivity on a small area of skin.
Do not use on damaged skin. Use only as directed. Avoid
contact with eyes.Rinse with warm water to remove. Stop
use and consult your physician it rash occurs. Do not ingest.
lf swallowed, get medical help or contact a Poison Control
Center right away! Do not use if safety seal is breken or
missing. Store in a cool, dry place.

When Using

When using this product keep out of
eyes, ears, and mouth, In case of contact
with eyes,rinse eyes thoroughly with
water. Stop use and ask a doctor if
irritation or rash occurs. These may be
signs of a serious condition.Keep out of
reach of children. If swallowed, get
medical help or contact a Poison Control
Center right away.

Keep Out Of Reach Of Children

Directions Of Safe Use:

Make Sure The Application,Area Is Clean And Dry, Apply a
Thin Layer And Massage Gently Into Your Skin Until Fully
Absorbed, Keep Treated Skin Covered From Sunlight And
Follow Up With Spf 30+ Sunscreen, For Better Results,
Use Pearl Bright Once a Day.

Inactive ingredients

Water, Sunflower Oil, Esters of Caprylic and Capric Acids,
Trideceth-6, Aloe Vera, Niacinamide, Glycyrrhiza Glabra
(Licorice) Extract, Morus Alba Root (Mulberry) Extract,
Hydrolyzed Oat Protein Ethyl Ascorbic Acid,
Hyaluronic Acid, Phenoxyethanol, Green Tea Extract,
Tetrapeptide-21, Collagen, Tocopherol, Potassium Sorbate,
Citric Acid, Lemon Essential Oil.